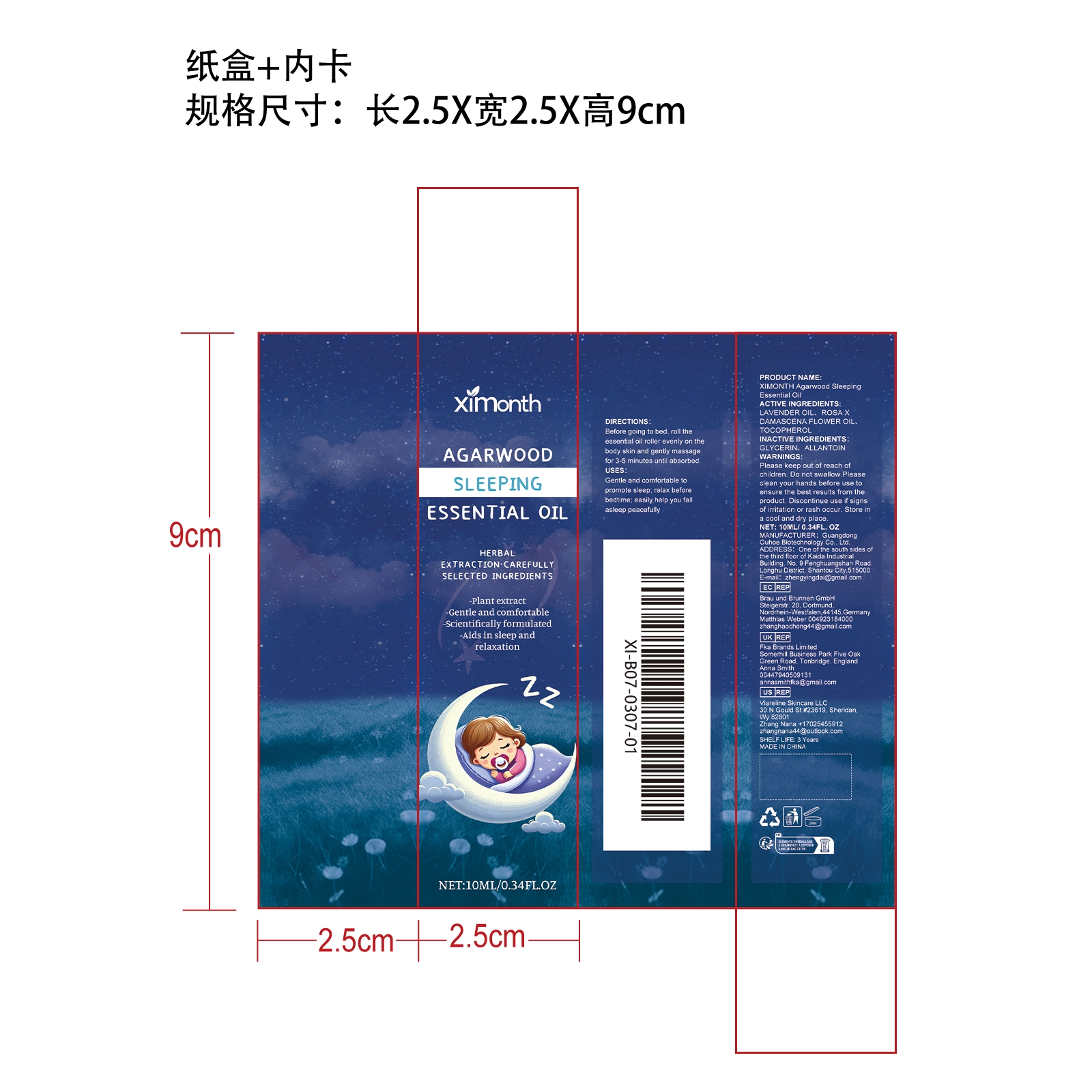 DRUG LABEL: XIMONTH Agarwood Sleeping Essential Oil
NDC: 84744-065 | Form: OIL
Manufacturer: Guangdong Ouhoe Biotechnology Co., Ltd.
Category: otc | Type: HUMAN OTC DRUG LABEL
Date: 20241024

ACTIVE INGREDIENTS: LAVENDER OIL 3 mg/10 mg; ROSA X DAMASCENA FLOWER OIL 1 mg/10 mg; TOCOPHEROL 1.5 mg/10 mg
INACTIVE INGREDIENTS: ALLANTOIN 3 mg/10 mg; GLYCERIN 1.5 mg/10 mg

ACTIVE INGREDIENTS

LAVENDER OIL、ROSA X DAMASCENA FLOWER OIL、TOCOPHEROL

PURPOSE

Gentle and comfortable to promote sleep; relax before bedtime; easily help you fall asleep peacefully

USE

Before going to bed, roll the essential oil roller evenly on the body skin and gently massage for 3-5 minutes until absorbed.

WARNINGS

Please keep out of reach of children. Do not swallow.Please clean your hands before use to ensure the best results from the product. Discontinue use if signs of irritation or rash occur. Store in a cool and dry place.

STOP USE

Discontinue use if signs of irritation or rash occur.

DO NOT USE

Discontinue use if signs of irritation or rash occur.

KEEP OUT OF REACH OF CHILDREN

Please keep out of reach of children. Do not swallow.

STORAGE AND HANDLING

Store in a cool and dry place.

INACTIVE INGREDIENT

GLYCERIN、ALLANTOIN